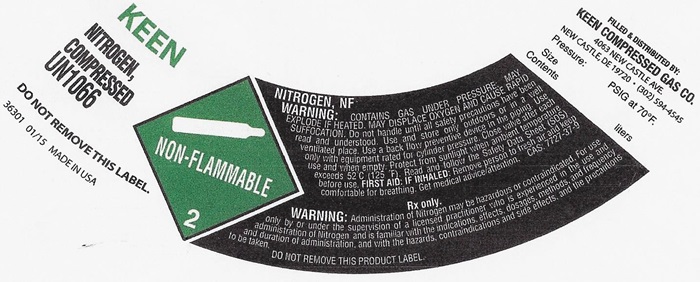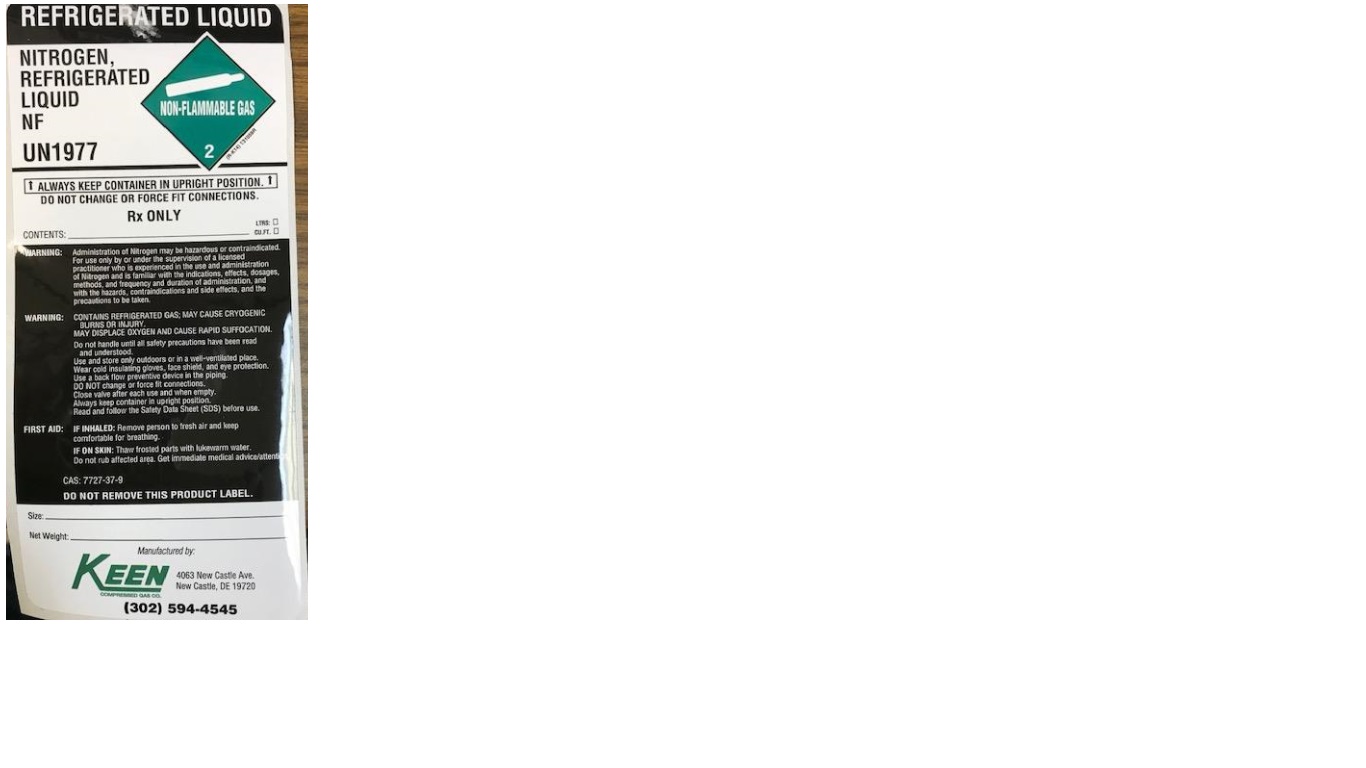 DRUG LABEL: NITROGEN
NDC: 48273-006 | Form: GAS
Manufacturer: Keen Compressed Gas Co. Inc.
Category: prescription | Type: HUMAN PRESCRIPTION DRUG LABEL
Date: 20251117

ACTIVE INGREDIENTS: NITROGEN 99 L/100 L

Nitrogen

HP NITROGEN COMPRESSED LABEL

KEEN

NITROGEN, COMPRESSED NF UN1066

DO NOT REMOVE THIS LABEL

36301 01/15 MADE IN USA

NON-FLAMMABLE GAS 2

NITROGEN, NF

WARNING: CONTAINS GAS UNDER PRESSURE; MAY EXPLODE, IF HEATED, MAY DISPLACE OXYGEN AND CAUSE RAPID SUFFOCCATION. Do not handle until all safety precautions have been read and understood. Use and store only outdoors or in a well-ventilated place. Use a back flow preventive device in the piping. Use only with equipment rated for cylinder pressure. Close valve after each use and when empty. Protect from sunlight when ambient temperature exceeds 52°C (125°F). Read and follow the Safety Data Sheet (SDS) before use. FIRST AID; IF INHALED; Remove person to fresh air and keep comfortable for breathing. Get medical advice/attention. CAS: 7727-37-9

Rx only.

WARNING: Administration of Nitrogen may be hazardous or contraindicated. For use only by or under the supervision of a licensed practioner who is experienced in the use and administration of Nitrogen and is familiar with the indications, effects, dosages, methods, and frequency and duration of administration, and with the hazards, contraindications and side effects and the precautions to be taken. DO NOT REMOVE THIS PRODUCT LABEL.

FILLED & DISTRIBUTED BY:

KEEN COMPRESSED GAS CO.

4063 NEW CASTLE AVE

NEW CASTEL, DE 19720 • (302) 594-4545

Pressure: PSIG at 70OF

Contents liters

PACKAGE LABEL

REFRIGERATED LIQUID

NITROGEN, REGRIGERATED LIQUID NF

UN1977

ALWAYS KEEP CONTAINER IN UPRIGHT POSITION.

DO NO CHANGE OR FORCE FIT CONNECTIONS.

Rx ONLY

CONTENTS: LTRS: CU.FT.

WARNING: Administration of Nitrogen may be hazardous or contraindicated. For use only by or under the supervision of a licensed practitioner who is experienced in the use and administration of Nitrogen and is familiar with the indications, effects, dosages, methods, and frequency and duration of administration, and with the hazards, contraindications and side effects, and the precautions to be taken.

WARNING: CONTAINS REFRIGERATED GAS; MAY CAUSE CRYOGENIC BURNS OR INJURY.

MAY DISPLACE OXYGEN AND CAUSE RAPID SUFFOCATION.

Do not handle until all safety precautions have been read and understood. Use and store only outdoors or in a well-ventilated place. Wear cold insulation gloves, face shield, and eye protection. Use a back flow preventive device in the piping. DO NOT change or force fit connections. Close valve after each use and when empty. Always keep container in upright position. Read and follow the Safety Data Sheet (SDS) before use.

FIRST AID: IF INHALED: Remove person to fresh air and keep comfortable for breathing.

IF ON SKIN: Thaw frosted parts with lukewarm water. Do not rub affected are. Get immediate medical advice/attention.

CAS: 7727-37-9

DO NOT REMOVE THIS PRODUCT LABEL.